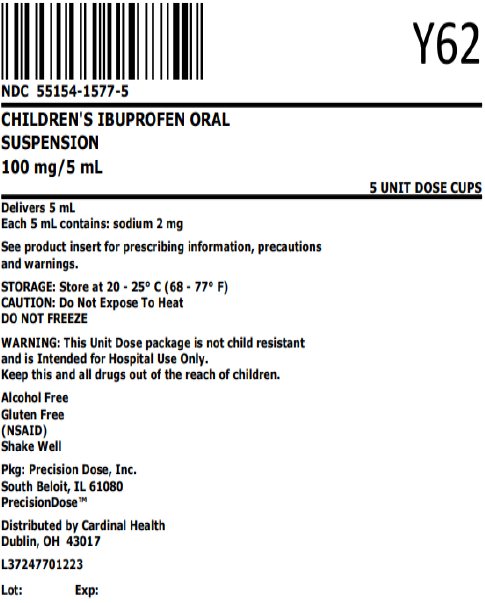 DRUG LABEL: Childrens Ibuprofen
NDC: 55154-1577 | Form: SUSPENSION
Manufacturer: Cardinal Health 107, LLC
Category: otc | Type: HUMAN OTC DRUG LABEL
Date: 20250822

ACTIVE INGREDIENTS: IBUPROFEN 100 mg/5 mL
INACTIVE INGREDIENTS: ANHYDROUS CITRIC ACID; D&C YELLOW NO. 10; FD&C RED NO. 40; GLYCERIN; HIGH FRUCTOSE CORN SYRUP; HYPROMELLOSE, UNSPECIFIED; POLYSORBATE 80; WATER; SODIUM BENZOATE; SORBITOL; XANTHAN GUM

CHILDREN'S IBUPROFEN ORAL SUSPENSION

Berry Flavor

100 mg/5 mL 200 mg/10 mL

For Hospital Use Only

LI1651 Rev. 02/25

Drug Facts

Active ingredient (in each 5 mL)

Ibuprofen 100 mg (NSAID) [nonsteroidal anti-inflammatory drug]

Purposes

Pain reliever/fever reducer

Uses

temporarily:

- relieves minor aches and pains due to the common cold, flu, sore throat, headache and toothache
- reduces fever

Warnings

Allergy alert

Ibuprofen may cause a severe allergic reaction, especially in people allergic to aspirin. Symptoms may include:

- hives
- facial swelling
- asthma (wheezing)
- shock
- skin reddening
- rash
- blisters

If an allergic reaction occurs, stop use and seek medical help right away.

Stomach bleeding warning

This product contains an NSAID, which may cause severe stomach bleeding. The chance is higher if your child:

- has had stomach ulcers or bleeding problems
- takes a blood thinning (anticoagulant) or steroid drug
- takes other drugs containing prescription or nonprescription NSAIDs (aspirin, ibuprofen, naproxen, or others)
- takes more or for a longer time than directed

Heart attack and stroke warning

NSAIDs, except aspirin, increase the risk of heart attack, heart failure, and stroke. These can be fatal. The risk is higher if you use more than directed or for longer than directed.

Sore throat warning

Severe or persistent sore throat or sore throat accompanied by high fever, headache, nausea, and vomiting may be serious. Consult doctor promptly. Do not use more than 2 days or administer to children under 3 years of age unless directed by doctor.

Do not use

- if the child has ever had an allergic reaction to ibuprofen or any other pain reliever/fever reducer
- right before or after heart surgery

Ask a doctor before use if

- stomach bleeding warning applies to your child
- child has a history of stomach problems, such as heartburn
- child has problems or serious side effects from taking pain relievers or fever reducers
- child has not been drinking fluids
- child has lost a lot of fluid due to vomiting or diarrhea
- child has high blood pressure, heart disease, liver cirrhosis, kidney disease, or had a stroke
- child has asthma
- child is taking a diuretic

Ask a doctor or pharmacist before use if the child is

- under a doctor's care for any serious condition
- taking any other drug

When using this product

- give with food or milk if stomach upset occurs

Stop use and ask a doctor if

- child experiences any of the following signs of stomach bleeding:
  - feels faint
  - vomits blood
  - has bloody or black stools
  - has stomach pain that does not get better
- child has symptoms of heart problems or stroke:
  - chest pain
  - trouble breathing
  - weakness in one part or side of body
  - slurred speech
  - leg swelling
- the child does not get any relief within first day (24 hours) of treatment
- fever or pain gets worse or lasts more than 3 days
- redness or swelling is present in the painful area
- any new symptoms appear

Keep out of reach of children. In case of overdose, get medical help or contact a Poison Control Center right away. (1-800-222-1222)

Directions

- Use as directed per healthcare professional.
- this product does not contain directions or complete warnings for adult use
- do not give more than directed
- shake well before using
- mL = milliliter
- find right dose on chart. If possible, use weight to dose; otherwise use age.
- if needed, repeat dose every 6-8 hours
- do not use more than 4 times a day

Dosing Chart
Weight (lb) | Age (yr) | Dose (mL) [or as directed by a doctor]
under 24 lbs | under 2 years | ask a doctor
24-35 lbs | 2-3 years | 5 mL
36-47 lbs | 4-5 years | 7.5 mL
48-59 lbs | 6-8 years | 10 mL
60-71 lbs | 9-10 years | 12.5 mL
72-95 lbs | 11 years | 15 mL

Other information

- each 5 mL contains: sodium 2 mg
- store at 20-25°C (68-77°F)
- do not freeze

Inactive ingredients

anhydrous citric acid, artificial mixed berry flavor, D&C yellow #10, FD&C red #40, glycerin, high fructose corn syrup, hypromellose, polysorbate 80, purified water, sodium benzoate, sorbitol solution, xanthan gum

Alcohol Free, Gluten Free

Questions or comments?

1-800-397-9228

How Supplied

Overbagged with 5 x 5 mL unit dose cups in each bag, NDC 55154-1577-5

WARNING: This Unit Dose package is not child resistant and is Intended for Institutional Use Only. Keep this and all drugs out of the reach of children.

Packaged By
Precision Dose, Inc.
South Beloit, IL 61080

For inquiries call Precision Dose, Inc. at 1-800-397-9228 or email
druginfo@precisiondose.com

Distributed By:

Cardinal Health

Dublin, OH 43017

L37247701223

LI1651 Rev. 02/25

Principal Display Panel

NDC 55154-1577-5

CHILDREN’S IBUPROFEN ORAL

SUSPENSION

100 mg/5 mL

5 UNIT DOSE CUPS